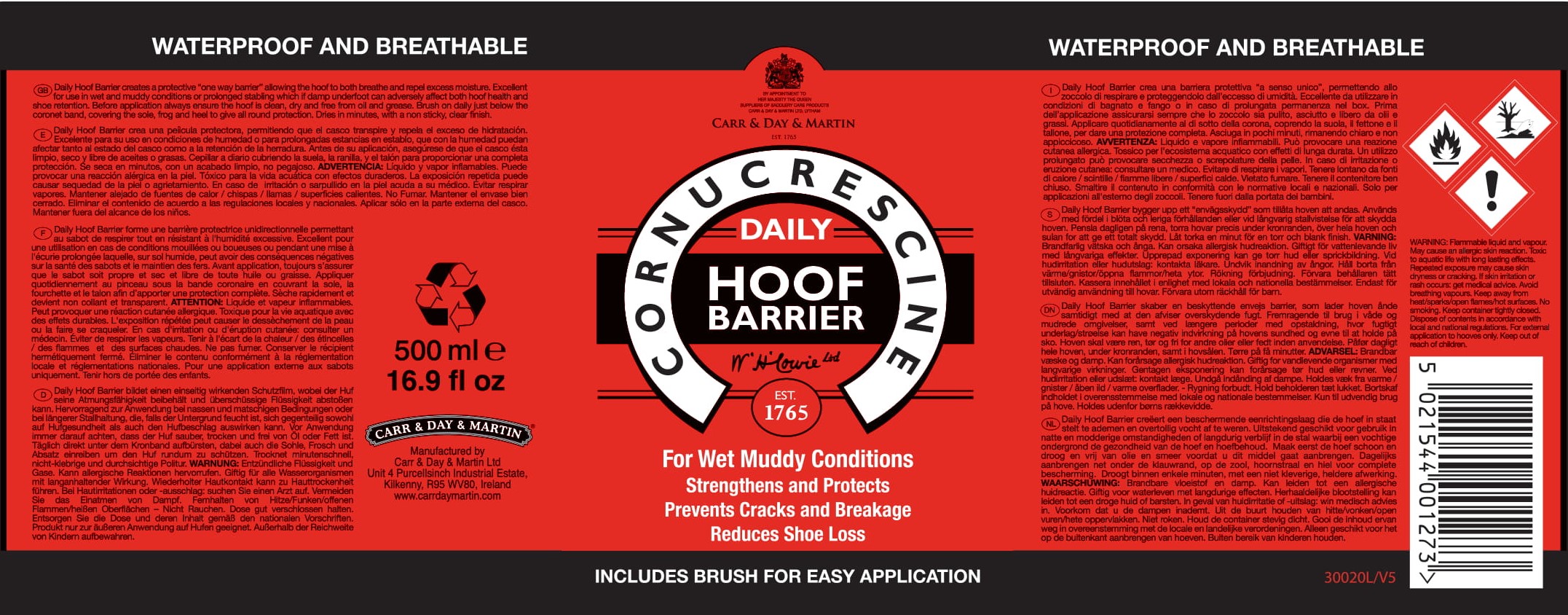 DRUG LABEL: Cornucrescine Daily Hoof Barrier
NDC: 43258-320 | Form: LIQUID
Manufacturer: Carr & Day & Martin Unlimited Company
Category: animal | Type: OTC ANIMAL DRUG LABEL
Date: 20250107

ACTIVE INGREDIENTS: WHITE SPIRIT TYPE 1 950 g/1 L; Turpentine 20 g/1 L

INDICATIONS AND USAGE

Daily Hoof Barrier creates a protective "one-way barrier" allowing the hoof to both breathe and repel excess moisture. Excellent for use in wet and muddy conditions or prolonged stabling which if damp underfoot can adversely affect both hoof health and shoe retention.

DOSAGE AND ADMINISTRATION

Before application always ensure the hoof is clean, dry and free from oil and grease. Brush on daily just below the coronet band, covering the sole, frog and heel to give all round protection. Dries in minutes, with a non sticky, clear finish.

Manufactured by

Carr & Day & Martin Unlimited Company

Unit 4 Purcellsinch Industrial Estate,

Kilkenny, R95 WV80, Ireland

www.carrdaymartin.com

WARNINGS AND PRECAUTIONS

Flammable IRRITANT

WARNING: Flammable liquid and vapour. May cause an allergic skin reaction. Toxic to aquatic life with long lasting effects. Repeated exposure may cause skin dryness or cracking. If skin irritation or rash occurs: get medical advice. Avoid breathing vapours. Keep away from heat/sparks/open flames/hot surfaces. No smoking. Keep container tightly closed. Dispose of contents in accordance with local and national regulations. For external application to hooves only. Keep out of reach of children.

Keep out of reach of children.